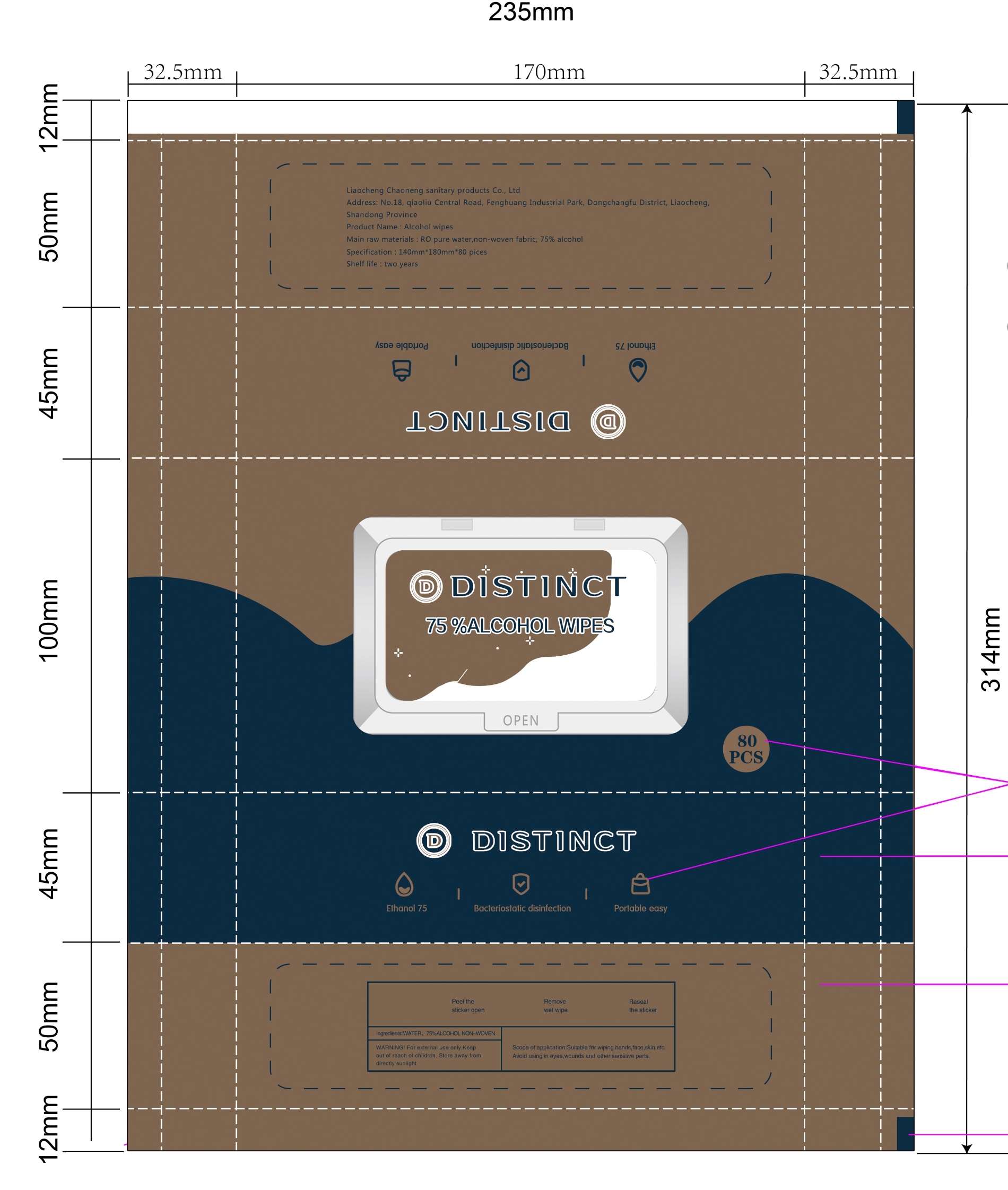 DRUG LABEL: Alcohol wipes
NDC: 55622-080 | Form: CLOTH
Manufacturer: Liaocheng Chaoneng Sanitary Products Co., Ltd.
Category: otc | Type: HUMAN OTC DRUG LABEL
Date: 20200920

ACTIVE INGREDIENTS: ALCOHOL 3.5 mL/1 1
INACTIVE INGREDIENTS: WATER

55622-080 ALCOHOL WIPES

Active Ingredient(s)

Alcohol 75% v/v. Purpose: Antiseptic

Purpose

Antiseptic,Alcohol wipes

Use

For cleaning and reducing germs and bacteria that could cause disease when soap & water are not available.

Warnings

For external use only. Flammable. Keep out of reach of children. Store away from directly sunlight.

Do not use

- in children less than 2 months of age
- on open skin wounds

When using this product keep out of eyes, ears, and mouth. In case of contact with eyes, rinse eyes thoroughly with water.
Stop use and ask a doctor if irritation or rash occurs. These may be signs of a serious condition.
Keep out of reach of children. If swallowed, get medical help or contact a Poison Control Center right away.

Stop use and ask a doctor if irritation or rash occurs. These may be signs of a serious condition.

Keep out of reach of children. If swallowed, get medical help or contact a Poison Control Center right away.

Directions

- Place enough product on hands to cover all surfaces. Rub hands together until dry.
- Supervise children under 6 years of age when using this product to avoid swallowing.

Other information

- Store between 15-30C (59-86F)
- Avoid freezing and excessive heat above 40C (104F)
  - Store away from directly sunlight

Inactive ingredients

purified water USP

Package Label - Principal Display Panel

80 cloth NDC: 55622-080-01